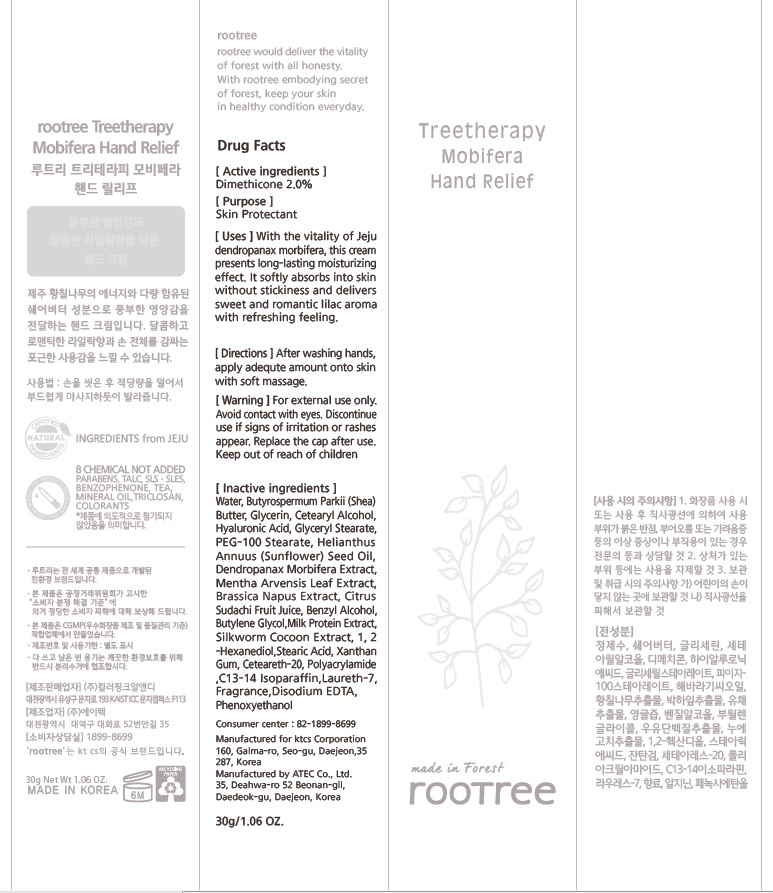 DRUG LABEL: rootree Treetherapy Mobifera Hand Relief
NDC: 72441-020 | Form: CREAM
Manufacturer: KTCS Corporation
Category: otc | Type: HUMAN OTC DRUG LABEL
Date: 20180730

ACTIVE INGREDIENTS: Dimethicone 0.6 g/30 g
INACTIVE INGREDIENTS: Water; SHEA BUTTER

ACTIVE INGREDIENT

Active ingredients: Dimethicone 2.0%

INACTIVE INGREDIENT

Inactive ingredients:

Water,Butyrospermum Parkii (Shea) Butter,Glycerin,Cetearyl Alcohol,Hyaluronic Acid,Glyceryl Stearate,PEG-100 Stearate,Helianthus Annuus (Sunflower) Seed Oil,Dendropanax Morbifera Extract,Mentha Arvensis Leaf Extract,Brassica Napus Extract,Citrus Sudachi Fruit Juice,Benzyl Alcohol,Butylene Glycol,Milk Protein Extract,Silkworm Cocoon Extract,1,2-Hexanediol,Stearic Acid,Xanthan Gum,Ceteareth-20,Polyacrylamide,C13-14 Isoparaffin,Laureth-7,Fragrance,Disodium EDTA,Phenoxyethanol

PURPOSE

Purpose: Skin Protectant

WARNINGS

For external use only.

Avoid contact with eyes.

Discontinue use if signs of irritation or rashes appear.

Replace the cap after use.

Keep out of reach of children

KEEP OUT OF REACH OF CHILDREN

Uses

With the vitality of Jeju dendropanax morbifera, this cream presents long-lasting moisturizing effect. It softly absorbs into skin without stickiness and delivers sweet and romantic lilac aroma with refreshing feeling.

Directions

After washing hands, apply adequte amount onto skin with soft massage.